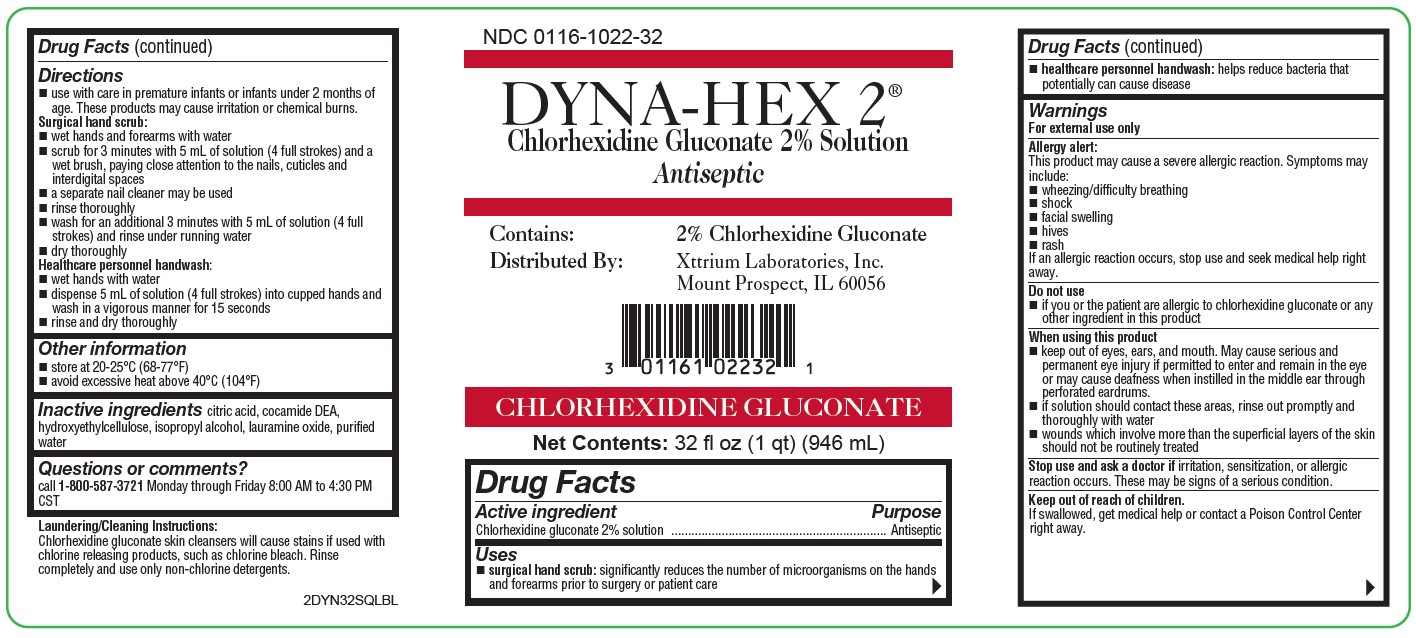 DRUG LABEL: Dyna-Hex 2
NDC: 0116-1022 | Form: SOLUTION
Manufacturer: Xttrium Laboratories, Inc.
Category: otc | Type: HUMAN OTC DRUG LABEL
Date: 20250430

ACTIVE INGREDIENTS: CHLORHEXIDINE GLUCONATE 20 mg/1 mL
INACTIVE INGREDIENTS: CITRIC ACID MONOHYDRATE; HYDROXYETHYL CELLULOSE (2000 MPA.S AT 1%); COCO DIETHANOLAMIDE; ISOPROPYL ALCOHOL; WATER; LAURAMINE OXIDE

Dyna-Hex 2% Square

Active Ingredient

Chlorhexidine gluconate 2% solution

Purpose

Antiseptic

Uses

- surgical hand scrub: significantly reduces the number of microorganisms on the hands and forearms prior to surgery or patient care
- healthcare personnel handwash: helps reduce bacteria that potentially can cause disease

WARNINGS

For external use only

Allergy alert:
This product may cause a severe allergic reaction. Symptoms may include:

 wheezing/difficulty breathing
 shock
 facial swelling
 hives
 rash
If an allergic reaction occurs, stop use and seek medical help right away.

Do not use

- if you or the patient are allergic to chlorhexidine gluconate or any other ingredient in this product

When using this product

 keep out of eyes, ears, and mouth. May cause serious and permanent eye injury if permitted to enter and remain in the eye or may cause deafness when instilled in the middle ear through perforated eardrums.
 if solution should contact these areas, rinse out promptly and thoroughly with water
 wounds which involve more than the superficial layers of the skin should not be routinely treated

Stop use and ask a doctor if

irritation, sensitization, or allergic reaction occurs. These may be signs of a serious condition.

Keep out of reach of children

if swallowed, get medical help or contact a Poison Control Center right away.

Directions

use with care in premature infants or infants under 2 months of age. These products may cause irritation or chemical burns.
Surgical hand scrub:
 wet hands and forearms with water
 scrub for 3 minutes with 5 mL of solution (4 full strokes) and a wet brush, paying close attention to the nails, cuticles and interdigital spaces
 a separate nail cleaner may be used
 rinse thoroughly
 wash for an additional 3 minutes with 5 mL of solution (4 full strokes) and rinse under running water
 dry thoroughly
Healthcare personnel handwash:
 wet hands with water
 dispense 5 mL of solution (4 full strokes) into cupped hands and wash in a vigorous manner for 15 seconds
 rinse and dry thoroughly

Other information

 store at 20-25°C (68-77°F)
 avoid excessive heat above 40°C (104°F)

INACTIVE INGREDIENT

citric acid, cocamide DEA, hydroxyethylcellulose, isopropyl alcohol, lauramine oxide, purified water

Questions or comments?

call 1-800-587-3721 Monday through Friday 8:00 AM to 4:30 PM CST

Laundering/Cleaning Instructions:

Chlorhexidine gluconate skin cleansers will cause stains if used with chlorine releasing products, such as chlorine bleach. Rinse completely and use only non-chlorine detergents.

PACKAGE LABEL

NDC 0116-1022-32

DYNA-HEX 2®

Chlorhexidine Gluconate 2% Solution Antiseptic

Contains: 2% Chlorhexidine Gluconate

Distributed By: Xttrium Laboratories, Inc. Mount Prospect, IL 60056

CHLORHEXIDINE GLUCONATE
Net Contents: 32 fl oz (1 qt) (946 mL)

2DYN32SQLBL